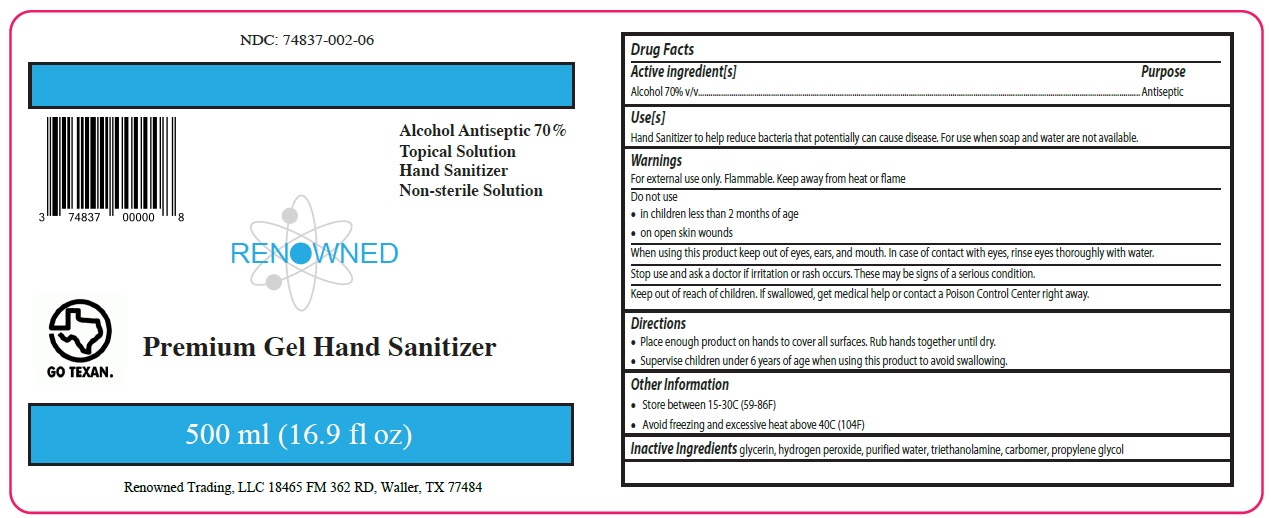 DRUG LABEL: Premium Hand Sanitizer Gel
NDC: 74837-002 | Form: GEL
Manufacturer: Renowned Chemical Solutions Llc
Category: otc | Type: HUMAN OTC DRUG LABEL
Date: 20200610

ACTIVE INGREDIENTS: ALCOHOL 70 mL/100 mL
INACTIVE INGREDIENTS: GLYCERIN; HYDROGEN PEROXIDE; WATER; TROLAMINE; CARBOMER HOMOPOLYMER, UNSPECIFIED TYPE; PROPYLENE GLYCOL

RENOWNED Premium Gel Hand Sanitizer

Active ingredient[s]

Alcohol 70% v/v

Purpose

Antiseptic

Use[s]

Hand Sanitizer to help reduce bacteria that potentially can cause disease. For use when soap and water are not available.

Warnings

For external use only. Flammable. Keep away from heat or flame

Do not use

• in children less than 2 months of age

• on open skin wounds

When using this product keep out of eyes, ears, and mouth. In case of contact with eyes, rinse eyes thoroughly with water.

Stop use and ask a doctor if irritation or rash occurs. These may be signs of a serious condition.

Keep out of reach of children. If swallowed, get medical help or contact a Poison Control Center right away.

Directions

• Place enough product on hands to cover all surfaces. Rub hands together until dry.

• Supervise children under 6 years of age when using this product to avoid swallowing.

Other Information

• Store between 15-30°C (59-86°F)

• Avoid freezing and excessive heat above 40°C (104°F)

INACTIVE INGREDIENT

Inactive Ingredients glycerin, hydrogen peroxide, purified water, triethanolamine, carbomer, propylene glycol

Alcohol Antiseptic 70%

Topical Solution

Hand Sanitizer

Non-sterile Solution

Renowned Trading, LLC 18465 FM 362 RD, Waller, TX 77484